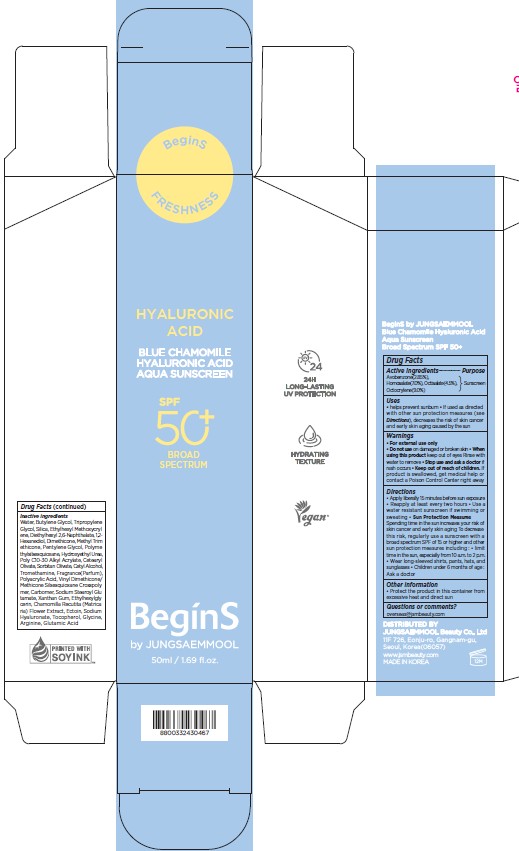 DRUG LABEL: BeginS by JUNGSAEMMOOL Blue Chamomile Hyaluronic Acid Aqua Sunscreen Broad Spectrum SPF 50 plus
NDC: 71261-040 | Form: CREAM
Manufacturer: Jungsaemmool Beauty Co., Ltd.
Category: otc | Type: HUMAN OTC DRUG LABEL
Date: 20260124

ACTIVE INGREDIENTS: AVOBENZONE 28.5 mg/1 mL; HOMOSALATE 70 mg/1 mL; OCTISALATE 45 mg/1 mL; OCTOCRYLENE 90 mg/1 mL
INACTIVE INGREDIENTS: WATER; BUTYLENE GLYCOL; TRIPROPYLENE GLYCOL; SILICON DIOXIDE; ETHYLHEXYL METHOXYCRYLENE; DIETHYLHEXYL 2,6-NAPHTHALATE; 1,2-HEXANEDIOL; DIMETHICONE, UNSPECIFIED; METHYL TRIMETHICONE; PENTYLENE GLYCOL; POLYMETHYLSILSESQUIOXANE (4.5 MICRONS); HYDROXYETHYL UREA; BEHENYL ACRYLATE POLYMER; CETEARYL OLIVATE; SORBITAN OLIVATE; CETYL ALCOHOL; TROMETHAMINE; POLYACRYLIC ACID (8000 MW); VINYL DIMETHICONE/METHICONE SILSESQUIOXANE CROSSPOLYMER; CARBOMER HOMOPOLYMER, UNSPECIFIED TYPE; SODIUM STEAROYL GLUTAMATE; XANTHAN GUM; ETHYLHEXYLGLYCERIN; CHAMOMILE; ECTOINE; LINALOOL, (+/-)-; LIMONENE, (+)-; HYALURONATE SODIUM; TOCOPHEROL; GLYCINE; ARGININE; GLUTAMIC ACID

71261-040_BeginS by JUNGSAEMMOOL Blue Chamomile Hyaluronic Acid Aqua Sunscreen Broad Spectrum SPF 50 plus

KEEP OUT OF REACH OF CHILDREN

Keep out of reach of the children. If product is swallowed, get medical help or contact a poison control center right away.

ACTIVE INGREDIENT

Avobenzone 2.85%

Homosalate 7.0%

Octisalate 4.5%

Octocrylene 9.0%

PURPOSE

Sunscreen

INDICATIONS AND USAGE

helps prevent sunburn

If used as directed with other sun protection measures (see Directions), decreases the risk of skin cancer and early skin aging caused by the sun

WARNINGS

For external use only

Do not use on damaged or broken skin

When using this product, keep out of eyes. Rinse with water to remove.

Stop using and ask a doctor if rash occurs.

DOSAGE AND ADMINISTRATION

Apply liberally 15 minutes before sun exposure. Reapply at least every two hours

Use a water resistant sunscreen if swimming or sweating

Sun protection measures. Spending time in the sun increases your risk of skin cancer and early skin aging. To decrease this risk, regularly use a sunscreen with a broad spectrum SPF of 15 or higher and other sun protection measures including: - Limit time in the sun, especially from 10 am to 2 pm. - Wear long-sleeve shirts, pants, hats, and sunglasses

Children under 6 months of age: Ask a doctor

INACTIVE INGREDIENT

Water, Butylene Glycol, Tripropylene Glycol, Silica, Ethylhexyl Methoxycrylene, Diethylhexyl 2,6-Naphthalate, 1,2-Hexanediol, Dimethicone, Methyl Trimethicone, Pentylene Glycol, Polymethylsilsesquioxane, Hydroxyethyl Urea, Poly C10-30 Alkyl Acrylate, Cetearyl Olivate, Sorbitan Olivate, Cetyl Alcohol, Tromethamine, Fragrance(Parfum), Polyacrylic Acid, Vinyl Dimethicone/Methicone Silsesquioxane Crosspolymer, Carbomer, Sodium Stearoyl Glutamate, Xanthan Gum, Ethylhexylglycerin, Chamomilla Recutita (Matricaria) Flower Extract, Ectoin, Linalool, Limonene, Sodium Hyaluronate, Tocopherol, Glycine, Arginine, Glutamic Acid

OTHER SAFETY INFORMATION

Protect the product in the container from excessive heat and direct sun